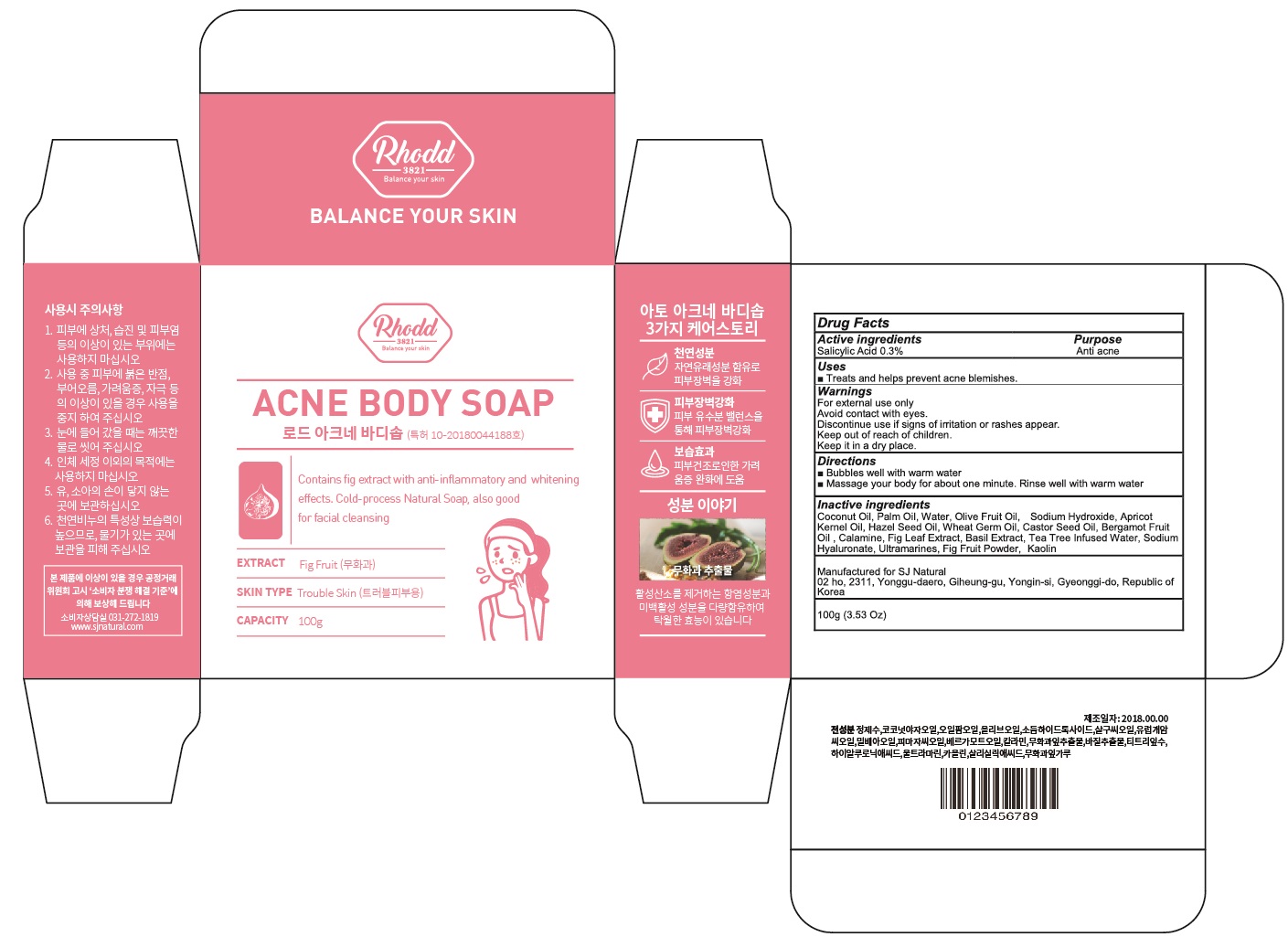 DRUG LABEL: RHODD ACNE BODY SO AP
NDC: 72535-020 | Form: SOAP
Manufacturer: SJ NATURAL
Category: otc | Type: HUMAN OTC DRUG LABEL
Date: 20180904

ACTIVE INGREDIENTS: SALICYLIC ACID 0.3 g/100 g
INACTIVE INGREDIENTS: COCONUT OIL; PALM OIL

ACTIVE INGREDIENT

Active ingredients: Salicylic Acid 0.3%

INACTIVE INGREDIENT

Inactive ingredients:

Inactive ingredients: Coconut Oil, Palm Oil, Water, Olive Fruit Oil, Sodium Hydroxide, Apricot Kernel Oil, Hazel Seed Oil, Wheat Germ Oil, Castor Seed Oil, Bergamot Fruit Oil , Calamine, Fig Leaf Extract, Basil Extract, Tea Tree Infused Water, Sodium Hyaluronate, Ultramarines, Fig Fruit Powder, Kaolin

PURPOSE

Purpose: Anti acne

WARNINGS

For external use only

Avoid contact with eyes.

Discontinue use if signs of irritation or rashes appear.

Keep out of reach of children.

Keep it in a dry place.

KEEP OUT OF REACH OF CHILDREN

Uses

Treats and helps prevent acne blemishes.

Directions

- Bubbles well with warm water

- Massage your body for about one minute. Rinse well with warm water.